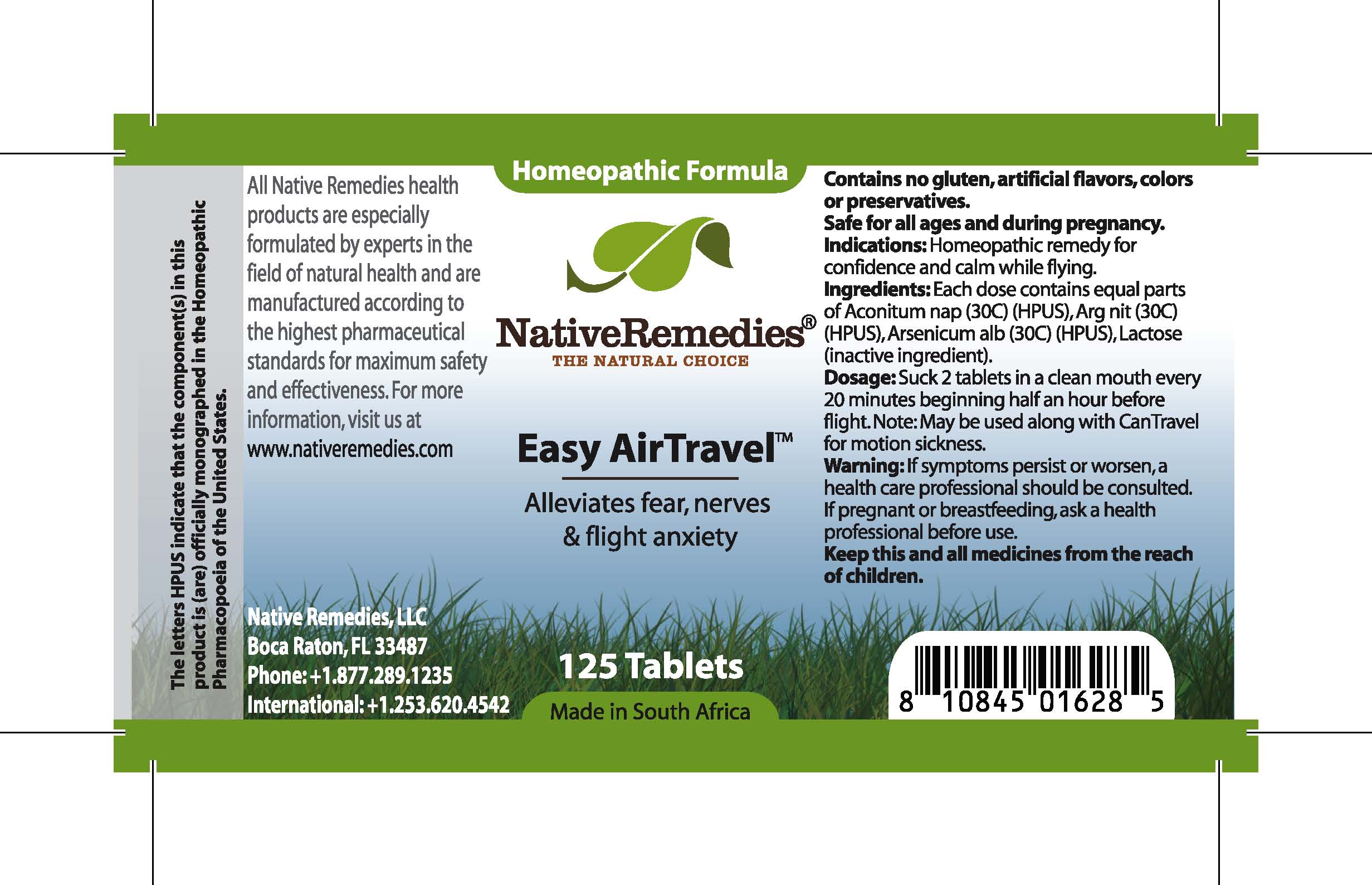 DRUG LABEL: Easy Air Travel
								
NDC: 68647-122 | Form: TABLET
Manufacturer: Feelgood Health
Category: homeopathic | Type: HUMAN OTC DRUG LABEL
Date: 20100616

ACTIVE INGREDIENTS: ACONITUM NAPELLUS 30 [hp_C]/1 1; SILVER NITRATE 30 [hp_C]/1 1; ARSENIC TRIOXIDE 30 [hp_C]/1 1

EASY AIR TRAVEL

DESCRIPTION

Alleviates fear, nerves and flight anxiety

INDICATIONS AND USAGE

Indications: Homeopathic remedy for confidence and calm while flying.

DOSAGE AND ADMINISTRATION

Dosage: Dissolve 2 tablets in a clean mouth every 20 minutes beginning half an hour before flight. May be used along with CanTravel™ for motion sickness.

GENERAL PRECAUTIONS

Caution: If symptoms persist or worsen, a health care professional should be consulted. Keep this and all medicines from the reach of children.

ACTIVE INGREDIENT

Ingredients: Each dose contains equal parts of Aconitum nap (30C) (HPUS), Arg nit (30C) (HPUS), Arsenicum alb (30C) (HPUS),

Lactose (inactive ingredient).

PREGNANCY

If pregnant or breastfeeding, ask a health professional before use.

USER SAFETY WARNINGS

Contains no gluten, artificial flavors, colors or preservatives. Safe for all ages and during pregnancy.

PATIENT COUNSELING INFORMATION

All Native Remedies health products are especially formulated by experts in the field of natural health and are manufactured according to the highest pharmaceutical standards for maximum safety and effectiveness. For more information, visit us at www.nativeremedies.com

Distributed by

Native Remedies, LLC

6531 Park of Commerce Blvd.

Suite 160

Boca Raton, FL 33487

Phone: 1.877.289.1235

International: + 1.561.999.8857

The letters HPUS indicate that the component(s) in this product is (are) officially monographed in the Homeopathic Pharmacopoeia of the United States.